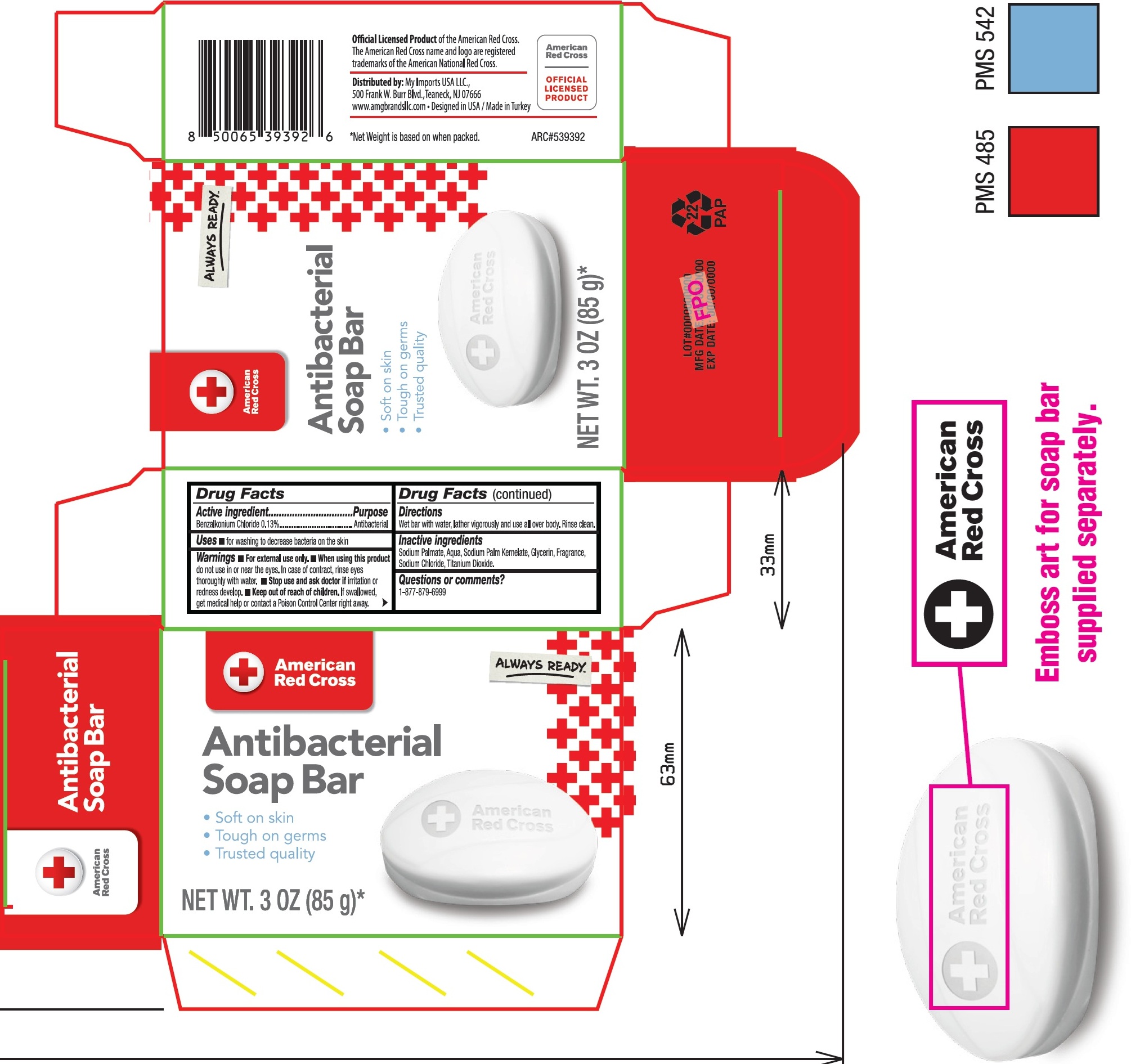 DRUG LABEL: American Red Cross Antibacterial Bar
NDC: 51628-0034 | Form: SOAP
Manufacturer: My Imports Usa, LLC
Category: otc | Type: HUMAN OTC DRUG LABEL
Date: 20260223

ACTIVE INGREDIENTS: BENZALKONIUM CHLORIDE 1.3 mg/1 g
INACTIVE INGREDIENTS: SODIUM PALMATE; WATER; SODIUM PALM KERNELATE; GLYCERIN; SODIUM CHLORIDE; TITANIUM DIOXIDE

American Red Cross Antibacterial Soap Bar

Active ingredient

Benzalkonium Chloride 0.13%

Purpose

Antibacterial

Uses

- for washing to decrease bacteria on the skin

Warnings

- For external use only.

When using this product

- do not use in or near the eyes. In case of contact, rinse eyes thoroughly with water.

Stop use and ask doctor if

- irritation or redness develop.

Keep out of reach of children.

- If swallowed, get medical help or contact a Poison Control Center right away.

Directions

Wet bar with water, lather vigorously and use all over body. Rinse clean.

Inacive ingredients

Sodium Palmate, Aqua, Sodium Palm Kernelate, Glycerin, Fragrance, Sodium Chloride, Titanium Dioxide.

Questions or comments?

1-877-879-6999